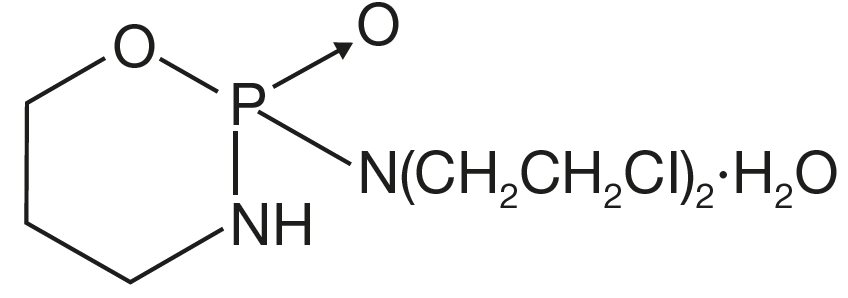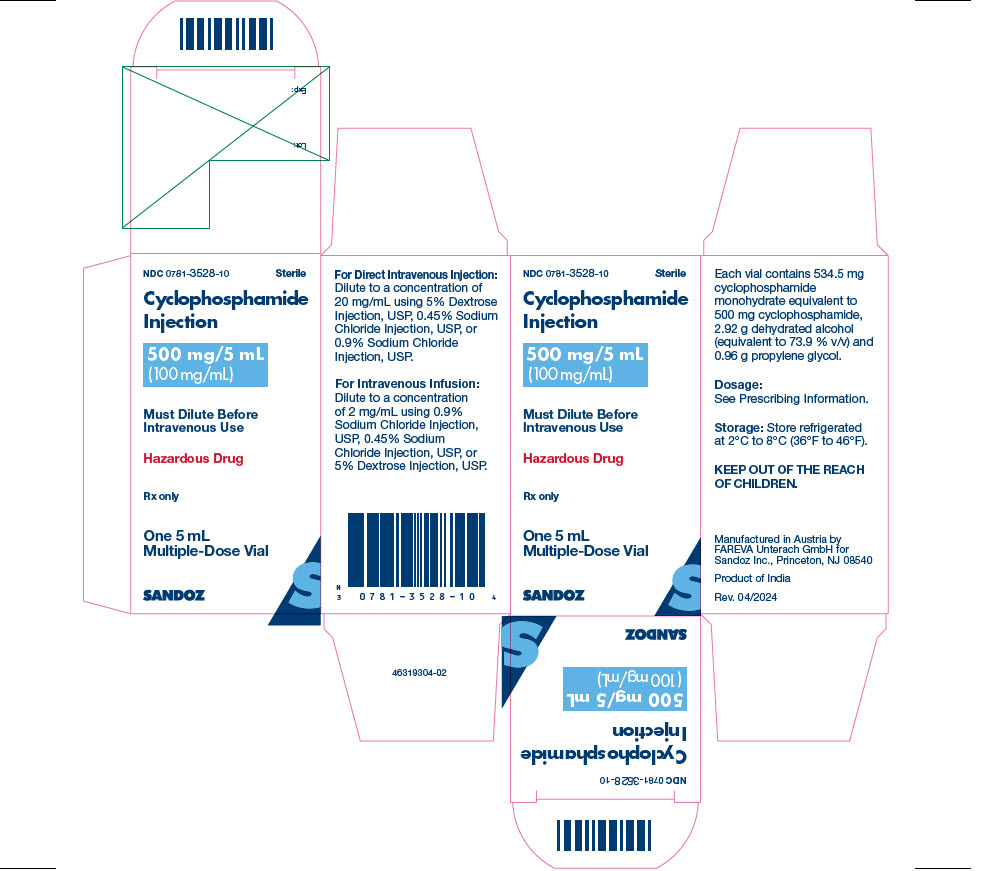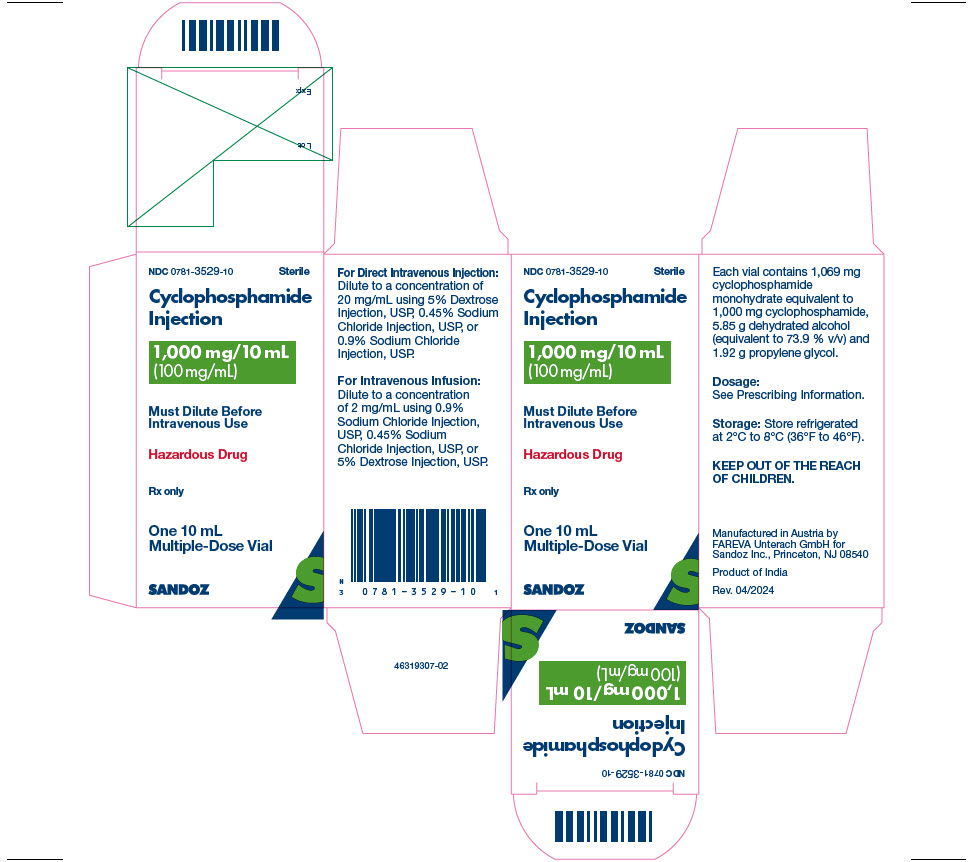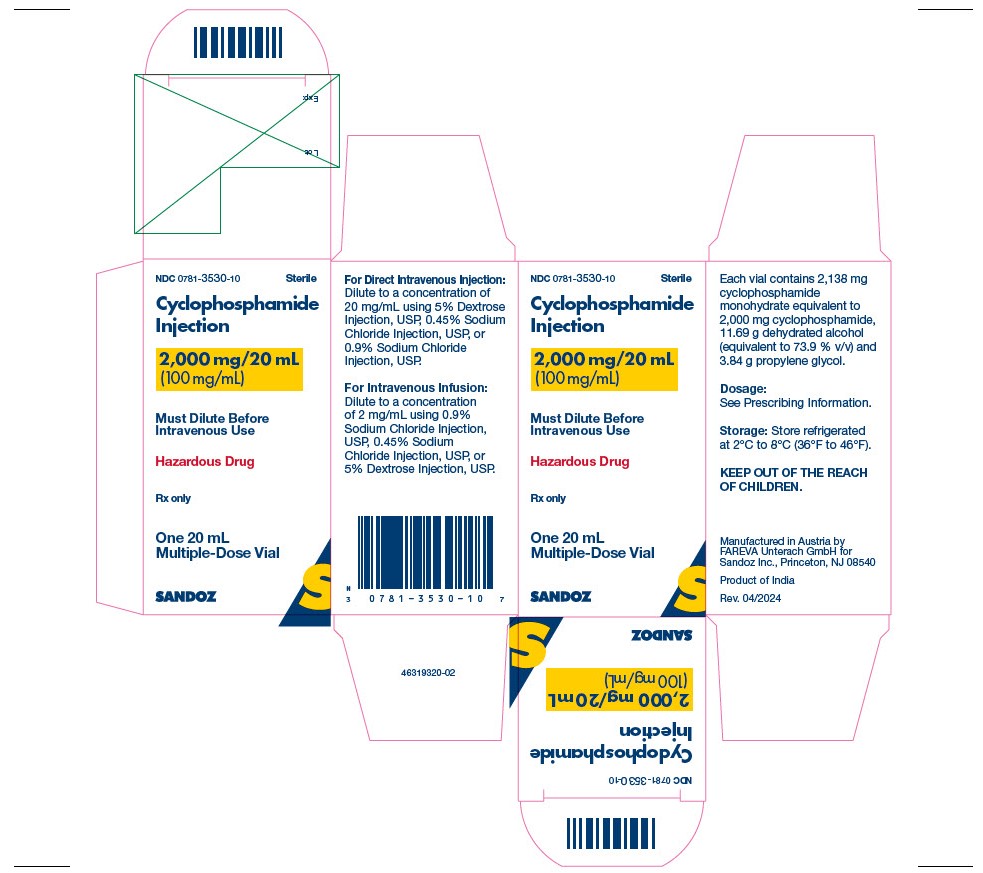 DRUG LABEL: Cyclophosphamide
NDC: 0781-3528 | Form: INJECTION, SOLUTION, CONCENTRATE
Manufacturer: Sandoz Inc
Category: prescription | Type: HUMAN PRESCRIPTION DRUG LABEL
Date: 20241230

ACTIVE INGREDIENTS: CYCLOPHOSPHAMIDE 500 mg/5 mL
INACTIVE INGREDIENTS: PROPYLENE GLYCOL; ALCOHOL

HIGHLIGHTS OF PRESCRIBING INFORMATION

These highlights do not include all the information needed to use CYCLOPHOSPHAMIDE INJECTION safely and effectively. See full prescribing information for CYCLOPHOSPHAMIDE INJECTION.
CYCLOPHOSPHAMIDE injection, for intravenous use
Initial U.S. Approval: 1959

RECENT MAJOR CHANGES

Dosage and Administration (2.2) 12/2024

1 INDICATIONS AND USAGE

Cyclophosphamide Injection is an alkylating drug indicated for treatment of adult patients with:

Malignant Diseases: malignant lymphomas: Hodgkin’s lymphoma, lymphocytic lymphoma, mixed-cell type lymphoma, histiocytic lymphoma, Burkitt’s lymphoma; multiple myeloma, leukemias, mycosis fungoides, neuroblastoma, adenocarcinoma of ovary, retinoblastoma, breast carcinoma. (1)

Limitations of Use

This cyclophosphamide product is not indicated for use in pediatric patients due to the alcohol and propylene glycol content in this product. If treatment with cyclophosphamide is indicated in a pediatric patient, use a different cyclophosphamide product. (1)

2 DOSAGE AND ADMINISTRATION

During or immediately after Cyclophosphamide Injection administration, administer adequate amounts of fluid to reduce the risk of urinary tract toxicity (2.1).

Malignant Diseases: Adult Patients (2.2)

- Intravenous: Initial course for patients with no hematologic deficiency: 40 mg/kg to 50 mg/kg in divided doses over 2 to 5 days. Other regimens include 10 mg/kg to 15 mg/kg given every 7 to 10 days or 3 mg/kg to 5 mg/kg twice weekly. (2.2)
- See full prescribing information for instructions on preparation, handling, and administration. (2.3)

3 DOSAGE FORMS AND STRENGTHS

Injection: 500 mg/5 mL (100 mg/mL), 1,000 mg/10 mL (100 mg/mL), 2,000 mg/20 mL (100 mg/mL) in multiple-dose vials (3)

4 CONTRAINDICATIONS

- Severe hypersensitivity to cyclophosphamide (4)
- Urinary outflow obstruction (4)

5 WARNINGS AND PRECAUTIONS

- Myelosuppression, Immunosuppression, Bone Marrow Failure, and Infections: Severe immunosuppression may lead to serious and sometimes fatal infections. Close hematological monitoring is required. (5.1)
- Urinary Tract and Renal Toxicity: Hemorrhagic cystitis, pyelitis, ureteritis, and hematuria can occur. Urotoxicity can be fatal. Exclude or correct any urinary tract obstructions prior to treatment. (5.2)
- Cardiotoxicity: Myocarditis, myopericarditis, pericardial effusion, arrythmias and congestive heart failure, which may be fatal, have been reported. Monitor patients, especially those with risk factors for cardiotoxicity or pre-existing cardiac disease. (5.3)
- Pulmonary Toxicity: Pneumonitis, pulmonary fibrosis and pulmonary veno-occlusive disease leading to respiratory failure may occur. Monitor patients for signs and symptoms of pulmonary toxicity. (5.4)
- Secondary Malignancies: Have been reported in patients treated with cyclophosphamide containing regimens. (5.5)
- Veno-occlusive Liver Disease: Fatal outcome can occur. (5.6)
- Alcohol Content: This product is not indicated for use in pediatric patients. The alcohol content in a dose of Cyclophosphamide Injection may affect the central nervous system. This may include impairment of a patient's ability to drive or use machines immediately after infusion. (5.7)
- Embryo-Fetal Toxicity: Can cause fetal harm. Advise females of reproductive potential of potential risk to a fetus and to use effective contraception. Advise males with female partners of reproductive potential to use effective contraception (5.8, 8.1, 8.3)

6 ADVERSE REACTIONS

The most common adverse reactions are neutropenia, febrile neutropenia, fever, alopecia, nausea, vomiting, and diarrhea. (6.1)

To report SUSPECTED ADVERSE REACTIONS, contact Sandoz Inc. at 1-800-525-8747 or FDA at 1-800-FDA-1088 or www.fda.gov/medwatch.

8 USE IN SPECIFIC POPULATIONS

- Lactation: Advise not to breastfeed. (8.2)
- Renal Impairment: Monitor for toxicity in patients with moderate and severe renal impairment. (8.6, 12.3)

FULL PRESCRIBING INFORMATION

1 INDICATIONS AND USAGE

Malignant Diseases

Cyclophosphamide Injection is indicated for the treatment of adult patients with:

- malignant lymphomas (Stages III and IV of the Ann Arbor staging system), Hodgkin’s lymphoma, lymphocytic lymphoma (nodular or diffuse), mixed-cell type lymphoma, histiocytic lymphoma, Burkitt’s lymphoma
- multiple myeloma
- leukemias: Chronic lymphocytic leukemia, chronic granulocytic leukemia (it is usually ineffective in acute blastic crisis), acute myelogenous and monocytic leukemia, acute lymphoblastic (stem-cell) leukemia (cyclophosphamide given during remission is effective in prolonging its duration)
- mycosis fungoides (advanced disease)
- neuroblastoma (disseminated disease)
- adenocarcinoma of the ovary
- retinoblastoma
- carcinoma of the breast

Cyclophosphamide, although effective alone in susceptible malignancies, is more frequently used concurrently or sequentially with other antineoplastic drugs.

Limitations of Use

This cyclophosphamide product is not indicated for use in pediatric patients due to the to the alcohol and propylene glycol content in this product. If treatment with cyclophosphamide is indicated in a pediatric patient, use a different cyclophosphamide product [see Warnings and Precautions (5.7), Use in Specific Populations (8.4), and Description (11)].

2 DOSAGE AND ADMINISTRATION

2.1 Important Administration Information

During or immediately after the administration, adequate amounts of fluid should be ingested or infused to force diuresis in order to reduce the risk of urinary tract toxicity. Therefore, Cyclophosphamide Injection should be administered in the morning.

2.2 Recommended Dosage for Malignant Diseases

Intravenous Use

When used as the only oncolytic drug therapy, the recommended dosage for the initial course of Cyclophosphamide Injection for patients with no hematologic deficiency is 40 mg per kg to 50 mg per kg given intravenously in divided doses over a period of 2 to 5 days. Other intravenous regimens include 10 mg per kg to 15 mg per kg given every 7 to 10 days or 3 mg per kg to 5 mg per kg twice weekly.

Adjust the dosage of Cyclophosphamide Injection based on the specific regimen administered, response to treatment, myelosuppression or other adverse reactions, and patient risk factors [see Warnings and Precautions (5)].

2.3 Preparation, Handling and Administration

Cyclophosphamide Injection is a hazardous drug. Follow applicable special handling and disposal procedures^1. Caution should be exercised when handling and preparing Cyclophosphamide Injection. To minimize the risk of dermal exposure, always wear gloves when handling vials containing Cyclophosphamide Injection.

Cyclophosphamide Injection

Intravenous Administration

Parenteral drug products should be inspected visually for particulate matter and discoloration prior to administration, whenever solution and container permit. Do not use Cyclophosphamide Injection vials if there are signs of particulate matter.

Cyclophosphamide Injection does not contain any antimicrobial preservative and thus care must be taken to assure the sterility of prepared solutions. Use aseptic technique.

For Direct Intravenous Injection

Aseptically withdraw the prescribed dose from the vial and dilute to a concentration of 20 mg/mL by using any of the following diluents:

- 5% Dextrose Injection
- 0.45% Sodium Chloride Injection
- 0.9% Sodium Chloride Injection

For Intravenous Infusion

Aseptically withdraw the prescribed dose from the vial and dilute to a concentration of 2 mg/mL by using any of the following diluents:

- 0.9% Sodium Chloride Injection
- 0.45% Sodium Chloride Injection
- 5% Dextrose Injection

To reduce the likelihood of adverse reactions that appear to be administration rate dependent (e.g., facial swelling, headache, nasal congestion, scalp burning), Cyclophosphamide Injection should be injected or infused very slowly. Duration of the infusion also should be appropriate for the volume and type of carrier fluid to be infused. Each vial is recommended for no more than a total of eight (8) dose withdrawals.

Storage of Diluted Cyclophosphamide Injection Solution:

If the diluted solution is not used immediately, store at room temperature at 68°F to 77°F (20°C to 25°C) for up to 24 hours or refrigerated at 36°F to 46°F (2°C to 8°C) for up to 6 days.

Storage of Undiluted Cyclophosphamide Injection Solution:

After first use, the partially used vial should be stored in the refrigerator in the original carton at 2°C to 8°C (36ºF to 46°F) up to 28 days. Discard unused portion after 28 days.

3 DOSAGE FORMS AND STRENGTHS

Cyclophosphamide Injection is a 100 mg/mL sterile, clear, colorless to pale-yellow solution in a multiple-dose vial available in the following presentations:

- 500 mg/5 mL
- 1,000 mg/10 mL
- 2,000 mg/20 mL

4 CONTRAINDICATIONS

Severe Hypersensitivity
Cyclophosphamide Injection is contraindicated in patients who have a history of severe hypersensitivity reactions to cyclophosphamide, any of its metabolites, or to other components of the product. Anaphylactic reactions including death have been reported with cyclophosphamide. Cross-sensitivity with other alkylating agents can occur.

Urinary Outflow Obstruction

Cyclophosphamide Injection is contraindicated in patients with urinary outflow obstruction [see Warnings and Precautions (5.2)].

5 WARNINGS AND PRECAUTIONS

5.1 Myelosuppression, Immunosuppression, Bone Marrow Failure and Infections

Cyclophosphamide can cause myelosuppression (leukopenia, neutropenia, thrombocytopenia and anemia), bone marrow failure, and severe immunosuppression which may lead to serious and sometimes fatal infections, including sepsis and septic shock. Latent infections can be reactivated [see Adverse Reactions (6.2)].

Antimicrobial prophylaxis may be indicated in certain cases of neutropenia at the discretion of the managing physician. In case of neutropenic fever, antibiotic therapy is indicated. Antimycotics and/or antivirals may also be indicated.

Monitoring of complete blood counts is essential during cyclophosphamide treatment so that the dose can be adjusted, if needed. Cyclophosphamide Injection should not be administered to patients with neutrophils ≤1,500/mm3 and platelets < 50,000/mm^3. Cyclophosphamide Injection treatment may not be indicated, or should be interrupted, or the dose reduced, in patients who have or who develop a serious infection. G-CSF may be administered to reduce the risks of neutropenia complications associated with cyclophosphamide use. Primary and secondary prophylaxis with G-CSF should be considered in all patients considered to be at increased risk for neutropenia complications. The nadirs of the reduction in leukocyte count and thrombocyte count are usually reached in weeks 1 and 2 of treatment. Peripheral blood cell counts are expected to normalize after approximately 20 days. Bone marrow failure has been reported. Severe myelosuppression may be expected particularly in patients pretreated with and/or receiving concomitant chemotherapy and/or radiation therapy.

5.2 Urinary Tract and Renal Toxicity

Hemorrhagic cystitis, pyelitis, ureteritis, and hematuria have been reported with cyclophosphamide. Medical and/or surgical supportive treatment may be required to treat protracted cases of severe hemorrhagic cystitis. Discontinue Cyclophosphamide Injection therapy in case of severe hemorrhagic cystitis. Urotoxicity (bladder ulceration, necrosis, fibrosis, contracture and secondary cancer) may require interruption of cyclophosphamide treatment or cystectomy. Urotoxicity can be fatal. Urotoxicity can occur with short-term or long-term use of cyclophosphamide.

Before starting treatment, exclude or correct any urinary tract obstructions [see Contraindications (4)]. Urinary sediment should be checked regularly for the presence of erythrocytes and other signs of urotoxicity and/or nephrotoxicity. Cyclophosphamide Injection should be used with caution, if at all, in patients with active urinary tract infections. Aggressive hydration with forced diuresis and frequent bladder emptying can reduce the frequency and severity of bladder toxicity. Mesna has been used to prevent severe bladder toxicity.

5.3 Cardiotoxicity

Myocarditis, myopericarditis, pericardial effusion including cardiac tamponade, and congestive heart failure, which may be fatal, have been reported with cyclophosphamide therapy.

Supraventricular arrhythmias (including atrial fibrillation and flutter) and ventricular arrhythmias (including severe QT prolongation associated with ventricular tachyarrhythmia) have been reported after treatment with regimens that included cyclophosphamide.

The risk of cardiotoxicity may be increased with high doses of cyclophosphamide, in patients with advanced age, and in patients with previous radiation treatment to the cardiac region and/or previous or concomitant treatment with other cardiotoxic agents.

Particular caution is necessary in patients with risk factors for cardiotoxicity and in patients with pre-existing cardiac disease.

Monitor patients with risk factors for cardiotoxicity and with pre-existing cardiac disease.

5.4 Pulmonary Toxicity

Pneumonitis, pulmonary fibrosis, pulmonary veno-occlusive disease and other forms of pulmonary toxicity leading to respiratory failure have been reported during and following treatment with cyclophosphamide. Late onset pneumonitis (greater than 6 months after start of cyclophosphamide) appears to be associated with increased mortality. Pneumonitis may develop years after treatment with cyclophosphamide.

Monitor patients for signs and symptoms of pulmonary toxicity.

5.5 Secondary Malignancies

Cyclophosphamide is genotoxic [see Nonclinical Toxicology (13.1)]. Secondary malignancies (urinary tract cancer, myelodysplasia, acute leukemias, lymphomas, thyroid cancer, and sarcomas) have been reported in patients treated with cyclophosphamide-containing regimens. The risk of bladder cancer may be reduced by prevention of hemorrhagic cystitis.

5.6 Veno-occlusive Liver Disease

Veno-occlusive liver disease (VOD) including fatal outcome has been reported in patients receiving cyclophosphamide-containing regimens. A cytoreductive regimen in preparation for bone marrow transplantation that consists of Cyclophosphamide Injection in combination with whole-body irradiation, busulfan, or other agents has been identified as a major risk factor. VOD has also been reported to develop gradually in patients receiving long-term low-dose immunosuppressive doses of cyclophosphamide. Other risk factors predisposing to the development of VOD include preexisting disturbances of hepatic function, previous radiation therapy of the abdomen, and a low performance status.

5.7 Alcohol Content

Due to the alcohol and propylene glycol content of this product, this cyclophosphamide product is not indicated for use in pediatric patients [see Indications and Usage (1) and Use in Specific Populations (8.4)]. If treatment with cyclophosphamide is indicated for a pediatric patient, use a different cyclophosphamide product.

The alcohol content in a dose of Cyclophosphamide Injection may affect the central nervous system and should be taken into account for patients in whom alcohol intake should be avoided or minimized. Consideration should be given to the alcohol content in Cyclophosphamide Injection on the ability to drive or use machines immediately after the infusion. Each administration of this cyclophosphamide product at 25 mg/kg/day delivers 146.2 mg/kg of ethanol. For a patient with a BSA of 70 kg, this would deliver 10.23 grams of ethanol. Other cyclophosphamide products may have a different amount of alcohol or no alcohol.

Monitor patients for signs of alcohol intoxication during and after treatment. Counsel patients about the possible effects of the alcohol content in this cyclophosphamide product, including possible effects on the central nervous system.

5.8 Embryo-Fetal Toxicity

Based on its mechanism of action and published reports of effects in pregnant patients or animals, Cyclophosphamide Injection can cause fetal harm when administered to a pregnant woman [see Use in Specific Populations (8.1), Clinical Pharmacology (12.1), and Nonclinical Toxicology (13.1)]. Exposure to cyclophosphamide during pregnancy may cause birth defects, miscarriage, fetal growth retardation, and fetotoxic effects in the newborn. Cyclophosphamide is teratogenic and embryo-fetal toxic in mice, rats, rabbits, and monkeys.

Advise pregnant women and females of reproductive potential of the potential risk to a fetus [see Use in Specific Populations (8.1)]. Advise females of reproductive potential to use effective contraception during treatment with Cyclophosphamide Injection and for up to 1 year after completion of therapy. Advise male patients with female partners of reproductive potential to use effective contraception during treatment with Cyclophosphamide Injection and for 4 months after completion of therapy [see Use in Specific Populations (8.1, 8.3)].

5.9 Infertility

Male and female reproductive function and fertility may be impaired in patients being treated with Cyclophosphamide Injection. Cyclophosphamide interferes with oogenesis and spermatogenesis. It may cause sterility in both sexes. Development of sterility appears to depend on the dose of cyclophosphamide, duration of therapy, and the state of gonadal function at the time of treatment. Cyclophosphamide-induced sterility may be irreversible in some patients. Advise patients on the potential risks for infertility [see Use in Specific Populations (8.3, 8.4)].

5.10 Impairment of Wound Healing

Cyclophosphamide may interfere with normal wound healing.

5.11 Hyponatremia

Hyponatremia associated with increased total body water, acute water intoxication, and a syndrome resembling SIADH (syndrome of inappropriate secretion of antidiuretic hormone), which may be fatal, has been reported.

6 ADVERSE REACTIONS

The following adverse reactions are discussed in more detail in other sections of the labeling.

- Hypersensitivity [see Contraindications (4)]
- Myelosuppression, Immunosuppression, Bone Marrow Failure, and Infections [see Warnings and Precautions (5.1)]
- Urinary Tract and Renal Toxicity [see Warnings and Precautions (5.2)]
- Cardiotoxicity [see Warnings and Precautions (5.3)]
- Pulmonary Toxicity [see Warnings and Precautions (5.4)]
- Secondary Malignancies [see Warnings and Precautions (5.5)]
- Veno-occlusive Liver Disease [see Warnings and Precautions (5.6)]
- Alcohol Content [see Warnings and Precautions (5.7)]
- Infertility [see Warnings and Precautions (5.9)]
- Impaired Wound Healing [see Warnings and Precautions (5.10)]
- Hyponatremia [see Warnings and Precautions (5.11)]

6.1 Clinical Trials and Postmarketing Experience

The following adverse reactions associated with the use of cyclophosphamide were identified in clinical studies or postmarketing reports. Because some of these reactions were reported voluntarily from a population of uncertain size, it is not always possible to reliably estimate their frequency or establish a causal relationship to drug exposure.

The most common adverse reactions were neutropenia, febrile neutropenia, fever, alopecia, nausea, vomiting, and diarrhea.

Cardiac: cardiac arrest, ventricular fibrillation, ventricular tachycardia, cardiogenic shock, pericardial effusion (progressing to cardiac tamponade), myocardial hemorrhage, myocardial infarction, cardiac failure (including fatal outcomes), cardiomyopathy, myocarditis, pericarditis, carditis, atrial fibrillation, supraventricular arrhythmia, ventricular arrhythmia, bradycardia, tachycardia, palpitations, QT prolongation.

Congenital, Familial and Genetic: intra-uterine death, fetal malformation, fetal growth retardation, fetal toxicity (including myelosuppression, gastroenteritis).

Ear and Labyrinth: deafness, hearing impaired, tinnitus.

Endocrine: water intoxication.

Eye: visual impairment, conjunctivitis, lacrimation.

Gastrointestinal: gastrointestinal hemorrhage, acute pancreatitis, colitis, enteritis, cecitis, stomatitis, constipation, parotid gland inflammation, nausea, vomiting, diarrhea.

General Disorders and Administrative Site Conditions: multiorgan failure, general physical deterioration, influenza-like illness, injection/infusion site reactions (thrombosis, necrosis, phlebitis, inflammation, pain, swelling, erythema), pyrexia, edema, chest pain, mucosal inflammation, asthenia, pain, chills, fatigue, malaise, headache, febrile neutropenia.

Hematologic: myelosuppression, bone marrow failure, disseminated intravascular coagulation and hemolytic uremic syndrome (with thrombotic microangiopathy).

Hepatic: veno-occlusive liver disease, cholestatic hepatitis, cytolytic hepatitis, hepatitis, cholestasis; hepatotoxicity with hepatic failure, hepatic encephalopathy, ascites, hepatomegaly, blood bilirubin increased, hepatic function abnormal, hepatic enzymes increased.

Immune: immunosuppression, anaphylactic shock and hypersensitivity reaction.

Infections: The following manifestations have been associated with myelosuppression and immunosuppression caused by cyclophosphamide: increased risk for and severity of pneumonias (including fatal outcomes), other bacterial, fungal, viral, protozoal, and parasitic infections; reactivation of latent infections, (including viral hepatitis, tuberculosis), pneumocystis jiroveci, herpes zoster, strongyloides, sepsis and septic shock.

Investigations: blood lactate dehydrogenase increased, C-reactive protein increased.

Metabolism and Nutrition: hyponatremia, fluid retention, blood glucose increased, blood glucose decreased.

Musculoskeletal and Connective Tissue: rhabdomyolysis, scleroderma, muscle spasms, myalgia, arthralgia.

Neoplasms: acute leukemia, myelodysplastic syndrome, lymphoma, sarcomas, renal cell carcinoma, renal pelvis cancer, bladder cancer, ureteric cancer, thyroid cancer.

Nervous System: encephalopathy, convulsion, dizziness, neurotoxicity has been reported and manifested as reversible posterior leukoencephalopathy syndrome, myelopathy, peripheral neuropathy, polyneuropathy, neuralgia, dysesthesia, hypoesthesia, paresthesia, tremor, dysgeusia, hypogeusia, parosmia.

Pregnancy: premature labor.

Psychiatric: confusional state.

Renal and Urinary: renal failure, renal tubular disorder, renal impairment, nephropathy toxic, hemorrhagic cystitis, bladder necrosis, cystitis ulcerative, bladder contracture, hematuria, nephrogenic diabetes insipidus, atypical urinary bladder epithelial cells.

Reproductive System: infertility, ovarian failure, ovarian disorder, amenorrhea, oligomenorrhea, testicular atrophy, azoospermia, oligospermia.

Respiratory: pulmonary veno-occlusive disease, acute respiratory distress syndrome, interstitial lung disease as manifested by respiratory failure (including fatal outcomes), obliterative bronchiolitis, organizing pneumonia, alveolitis allergic, pneumonitis, pulmonary hemorrhage; respiratory distress, pulmonary hypertension, pulmonary edema, pleural effusion, bronchospasm, dyspnea, hypoxia, cough, nasal congestion, nasal discomfort, oropharyngeal pain, rhinorrhea.

Skin and Subcutaneous Tissue: toxic epidermal necrolysis, Stevens-Johnson syndrome, erythema multiforme, palmar-plantar erythrodysesthesia syndrome, radiation recall dermatitis, toxic skin eruption, urticaria, dermatitis, blister, pruritus, erythema, nail disorder, facial swelling, hyperhidrosis, alopecia.

Tumor lysis syndrome: like other cytotoxic drugs, cyclophosphamide may induce tumor-lysis syndrome and hyperuricemia in patients with rapidly growing tumors.

Vascular: pulmonary embolism, venous thrombosis, vasculitis, peripheral ischemia, hypertension, hypotension, flushing, hot flush.

7 DRUG INTERACTIONS

7.1 Effect of Other Drugs on Cyclophosphamide Exposure

Protease Inhibitors

Concomitant use of protease inhibitors may increase the concentration of cytotoxic metabolites and may enhance the toxicities of cyclophosphamide, including higher incidence of infections, neutropenia, and mucositis. Monitor for increased toxicities in patients receiving protease inhibitors.

7.2 Drugs that Potentiate Cyclophosphamide Toxicities

Radiation therapy or drugs with similar toxicities to Cyclophosphamide Injection can potentiate toxicities for cyclophosphamide. Monitor for increased toxicities in patients receiving radiation therapy or drugs known to cause:

- Myelosuppression and/or immunosuppression [see Warnings and Precautions (5.1)]
- Nephrotoxicity including hemorrhagic cystitis [see Warnings and Precautions (5.2)]
- Cardiotoxicity [see Warnings and Precautions (5.3)]
- Pulmonary toxicity [see Warnings and Precautions (5.4)]
- Secondary malignancies [see Warnings and Precautions (5.5)]
- Hepatotoxicity including liver necrosis and VOD [see Warnings and Precautions (5.6)]

7.3 Effect of Cyclophosphamide on Other Drugs

Metronidazole

Acute encephalopathy has been reported in a patient receiving cyclophosphamide and metronidazole. Monitor for neurologic toxicities in patients receiving metronidazole.

Tamoxifen

Concomitant use of tamoxifen and a cyclophosphamide-containing chemotherapy regimen may increase the risk of thromboembolic complications. Monitor for signs and symptoms of thromboembolic events in patients receiving tamoxifen.

Coumarins

Both increased and decreased warfarin effect have been reported in patients receiving warfarin and cyclophosphamide. Monitor anticoagulant activity closely in patients receiving warfarin or other coumarins.

Cyclosporine

Concomitant administration of cyclophosphamide may decrease serum concentrations of cyclosporine. This interaction may result in an increased incidence of graft-versus-host disease. Monitor for signs and symptoms of graft-versus-host disease in patients receiving cyclosporine.

Depolarizing muscle relaxants

If a patient has been treated with cyclophosphamide within 10 days of general anesthesia, alert the anesthesiologist.

Cyclophosphamide causes a marked and persistent inhibition of cholinesterase activity. Prolonged apnea may occur with concurrent depolarizing muscle relaxants (e.g., succinylcholine).

8 USE IN SPECIFIC POPULATIONS

8.1 Pregnancy

Risk Summary

Based on its mechanism of action and published reports of effects in pregnant patients or animals, Cyclophosphamide Injection can cause fetal harm when administered to a pregnant woman [see Clinical Pharmacology (12.1) and Nonclinical Toxicology (13.1)]. Exposure to cyclophosphamide during pregnancy may cause fetal malformations, miscarriage, fetal growth retardation, and toxic effects in the newborn [see Data]. Cyclophosphamide is teratogenic and embryo-fetal toxic in mice, rats, rabbits and monkeys [see Data]. Advise pregnant women and females of reproductive potential of the potential risk to the fetus.

The estimated background risk of major birth defects and miscarriage for the indicated population is unknown. In the U.S. general population, the estimated background risk of major birth defects is 2% to 4% and of miscarriage is 15% to 20% of clinically recognized pregnancies.

Data

Human Data

Malformations of the skeleton, palate, limbs and eyes as well as miscarriage have been reported after exposure to cyclophosphamide in the first trimester. Fetal growth retardation and toxic effects manifesting in the newborn, including leukopenia, anemia, pancytopenia, severe bone marrow hypoplasia, and gastroenteritis have been reported after exposure to cyclophosphamide.

Animal Data

Administration of cyclophosphamide to pregnant mice, rats, rabbits, and monkeys during the period of organogenesis at doses at or below the dose in patients based on body surface area resulted in various malformations, which included neural tube defects, limb and digit defects and other skeletal anomalies, cleft lip and palate, and reduced skeletal ossification.

8.2 Lactation

Risk Summary

Cyclophosphamide is present in breast milk. Neutropenia, thrombocytopenia, low hemoglobin, and diarrhea have been reported in infants breast fed by women treated with cyclophosphamide. Because of the potential for serious adverse reactions in a breastfed child, advise lactating women not to breastfeed during the treatment and for 1 week after the last dose.

8.3 Females and Males of Reproductive Potential

Cyclophosphamide Injection can cause fetal harm when administered to a pregnant woman [see Use in Specific Populations (8.1)].

Pregnancy Testing

Verify the pregnancy status of females of reproductive potential prior to the initiation of Cyclophosphamide Injection.

Contraception

Females

Advise female patients of reproductive potential to use effective contraception during treatment with Cyclophosphamide Injection and for up to 1 year after therapy.

Males

Based on findings in genetic toxicity and animal reproduction studies, advise male patients with female partners of reproductive potential to use effective contraception during treatment with Cyclophosphamide Injection for 4 months after therapy [see Nonclinical Toxicology (13.1)].

Infertility

Females
Amenorrhea, transient or permanent, associated with decreased estrogen and increased gonadotropin secretion develops in a proportion of women treated with cyclophosphamide. Affected patients generally resume regular menses within a few months after cessation of therapy. The risk of premature menopause with cyclophosphamide increases with age. Oligomenorrhea has also been reported in association with cyclophosphamide treatment.

Animal data suggest an increased risk of failed pregnancy and malformations may persist after discontinuation of cyclophosphamide as long as oocytes/follicles exist that were exposed to cyclophosphamide during any of their maturation phases. The exact duration of follicular development in humans is not known but may be longer than 12 months [see Nonclinical Toxicology (13.1)].

Males
Men treated with cyclophosphamide may develop oligospermia or azoospermia which are normally associated with increased gonadotropin but normal testosterone secretion.

8.4 Pediatric Use

This cyclophosphamide product is not indicated for use in pediatric patients due to the alcohol and propylene glycol content in this product. If treatment with cyclophosphamide is indicated in a pediatric patient, use a different cyclophosphamide product. Since propylene glycol and alcohol are both metabolized by the same enzymes, co-administration of these excipients may raise systemic exposure to alcohol, particularly in pediatric patients. [see Indications and Usage (1), Warnings and Precautions (5.7), and Description (11)]. Other cyclophosphamide products may have a different amount of alcohol or no alcohol.

Pre-pubescent girls treated with cyclophosphamide generally develop secondary sexual characteristics normally and have regular menses. Ovarian fibrosis with apparent complete loss of germ cells after prolonged cyclophosphamide treatment in late pre-pubescence has been reported. Girls treated with cyclophosphamide who have retained ovarian function after completing treatment are at increased risk of developing premature menopause.

Pre-pubescent boys treated with cyclophosphamide develop secondary sexual characteristics normally but may have oligospermia or azoospermia and increased gonadotropin secretion. Some degree of testicular atrophy may occur. Cyclophosphamide induced azoospermia is reversible in some patients, though the reversibility may not occur for several years after cessation of therapy.

8.5 Geriatric Use

There is insufficient data from clinical studies of cyclophosphamide available for patients 65 years of age and older to determine whether they respond differently than younger patients. In general, dose selection for an elderly patient should be cautious, usually starting at the low end of the dosing range, reflecting the greater frequency of decreased hepatic, renal, or cardiac functioning, and of concomitant disease or other drug therapy.

8.6 Renal Impairment

In patients with severe renal impairment, decreased renal excretion may result in increased plasma levels of cyclophosphamide and its metabolites. This may result in increased toxicity [see Clinical Pharmacology (12.3)]. Monitor patients with severe renal impairment (CLcr =10 mL/min to 24 mL/min) for signs and symptoms of toxicity.

Cyclophosphamide and its metabolites are dialyzable [see Clinical Pharmacology (12.3)] although there are probably quantitative differences depending upon the dialysis system being used. Use of a consistent interval between cyclophosphamide administration and dialysis should be considered in patients requiring dialysis.

8.7 Hepatic Impairment

Patients with severe hepatic impairment have reduced conversion of cyclophosphamide to the active 4-hydroxyl metabolite, potentially reducing efficacy [see Clinical Pharmacology (12.3)].

The alcohol content of Cyclophosphamide Injection should be taken into account when given to patients with hepatic impairment [see Warnings and Precautions (5.7)].

10 OVERDOSAGE

No specific antidote for cyclophosphamide is known.

Overdosage should be managed with supportive measures, including appropriate treatment for any concurrent infection, myelosuppression, or cardiac toxicity should it occur.

Serious consequences of overdosage include manifestations of dose dependent toxicities such as myelosuppression, urotoxicity, cardiotoxicity (including cardiac failure), veno-occlusive hepatic disease, and stomatitis [see Warnings and Precautions (5.1, 5.2, 5.3 and 5.6)].

Patients who received an overdose should be closely monitored for the development of toxicities, and hematologic toxicity in particular.

Cyclophosphamide and its metabolites are dialyzable. Therefore, rapid hemodialysis is indicated when treating any suicidal or accidental overdose or intoxication.

Cystitis prophylaxis with mesna may be helpful in preventing or limiting urotoxic effects with cyclophosphamide overdose.

11 DESCRIPTION

Cyclophosphamide is an alkylating drug. It is a synthetic antineoplastic drug chemically related to the nitrogen mustards. The chemical name for cyclophosphamide is 2-[bis(2-chloroethyl)amino]tetrahydro-2H-1,3,2-oxazaphosphorine 2-oxide monohydrate, and has the following structural formula:

Cyclophosphamide is a white crystalline powder with the molecular formula C7H15Cl2N2O2P•H2O and a molecular weight of 279.1. Cyclophosphamide is soluble in water and freely soluble in alcohol.

Cyclophosphamide Injection, 100 mg/mL is a sterile ready-to-dilute, clear, colorless to pale-yellow solution in a multiple-dose vial available as 500 mg/5 mL, 1,000 mg/10 mL, and 2,000 mg/20 mL strengths.

- 500 mg vial contains 534.5 mg cyclophosphamide monohydrate equivalent to 500 mg cyclophosphamide, 2.92 g dehydrated alcohol (equivalent to 73.9 % v/v) and 0.96 g propylene glycol.
- 1,000 mg vial contains 1,069 mg cyclophosphamide monohydrate equivalent to 1,000 mg cyclophosphamide, 5.85 g dehydrated alcohol (equivalent to 73.9 % v/v) and 1.92 g propylene glycol.
- 2,000 mg vial contains 2,138 mg cyclophosphamide monohydrate equivalent to 2,000 mg cyclophosphamide, 11.69 g dehydrated alcohol (equivalent to 73.9 % v/v) and 3.84 g propylene glycol.

12 CLINICAL PHARMACOLOGY

12.1 Mechanism of Action

The mechanism of action has not been fully characterized. However, cross-linking of tumor cell DNA may be involved.

The active alkylating metabolites of cyclophosphamide interfere with the growth of susceptible rapidly proliferating malignant cells.

12.2 Pharmacodynamics

Cyclophosphamide exposure-response relationships and the time course of pharmacodynamic response have not been fully characterized.

12.3 Pharmacokinetics

Cyclophosphamide is a prodrug. Cyclophosphamide pharmacokinetics are linear over the approved recommended dose range.

Distribution

The volume of distribution of cyclophosphamide is 30 to 50 L. Cyclophosphamide is approximately 20% protein bound, with no dose dependent changes. Some metabolites are greater than 60% protein bound.

Elimination

The elimination half-life (t½) of cyclophosphamide ranges from 3 to 12 hours, and clearance (CL) ranges from 4 to 5.6 L/h.

When cyclophosphamide was administered at 4 g/m^2 (approximately 2 times the approved recommended dosage) over a 90-minutes infusion, concentration-time data demonstrate saturable elimination in parallel with first-order renal elimination.

Metabolism

Cyclophosphamide is metabolized by cytochrome P450s including CYP2A6, 2B6, 3A, 2C9, and 2C19. Cyclophosphamide is activated to form 4-hydroxycyclophosphamide, which is in equilibrium with its ring-open tautomer aldophosphamide. 4-hydroxycyclophosphamide and aldophosphamide can undergo oxidation by aldehyde dehydrogenases to form the inactive metabolites 4-ketocyclophosphamide and carboxyphosphamide, respectively. Aldophosphamide can undergo β-elimination to form active metabolites phosphoramide mustard and acrolein. This spontaneous conversion can be catalyzed by albumin and other proteins. At high doses, the fraction of parent compound cleared by 4-hydroxylation is reduced resulting in non-linear elimination of cyclophosphamide.

Cyclophosphamide appears to induce its own metabolism. This auto-induction results in an increase in CL, increased formation of active 4-hydroxycyclophosphamide and shortened t½ following multiple doses administered at 12-to-24-hour interval.

Excretion

Cyclophosphamide and its metabolites are eliminated by hepatic and renal pathways. Cyclophosphamide is primarily excreted as metabolites. Ten to 20% is excreted unchanged in the urine. A small percentage of cyclophosphamide may be eliminated unchanged in bile.

Specific Populations

Renal Impairment

Following one-hour intravenous infusion, cyclophosphamide AUC increased by 38% in patients with CLcr of 25 to 50 mL/min, by 77% in patients with CLcr of 10 to 24 mL/min and by 23% in the hemodialysis group (CLcr of < 10 mL/min) compared to the control group (CLcr≥ 80 mL/min).

Cyclophosphamide is dialyzable. Dialysis clearance averaged 104 mL/min, which is similar to the metabolic clearance of 95 mL/min for cyclophosphamide. A mean of 37% of the administered dose of cyclophosphamide was removed during a 4-hour hemodialysis period. The t½ was 3.3 hours in patients during hemodialysis, a 49% reduction compared to t½ of 6.5 hours in uremic patients.

Hepatic Impairment

Cyclophosphamide CL is decreased by 40% (45 ± 8.6 L/kg) and t½ is prolonged by 64% (12.5 ± 1 hours) in patients with hepatic impairment with a mean bilirubin 3.5 mg/dL and mean AST 90 IU/L compared to patients with normal hepatic function (mean bilirubin 0.5 mg/dL, mean AST 10 IU/L).

13 NONCLINICAL TOXICOLOGY

13.1 Carcinogenesis, Mutagenesis, Impairment of Fertility

Cyclophosphamide administered by different routes, including intravenous, subcutaneous or intraperitoneal injection, or in drinking water, caused tumors in both mice and rats. In addition to leukemia and lymphoma, benign and malignant tumors were found at various tissue sites, including urinary bladder, mammary gland, lung, liver, and injection site [see Warnings and Precautions (5.5)].

Cyclophosphamide was mutagenic and clastogenic in multiple in vitro and in vivo genetic toxicology studies.

Cyclophosphamide is genotoxic in male and female germ cells. Animal data indicate that exposure of oocytes to cyclophosphamide during follicular development may result in a decreased rate of implantations and viable pregnancies, and in an increased risk of malformations. Male mice and rats treated with cyclophosphamide show alterations in male reproductive organs (e.g., decreased weights, atrophy, changes in spermatogenesis), and decreases in reproductive potential (e.g., decreased implantations and increased post-implantation loss) and increases in fetal malformations when mated with untreated females [see Use in Specific Populations (8.3)].

15 REFERENCES

1. OSHA Hazardous Drugs. OSHA. http://www.osha.gov/SLTC/hazardousdrugs/index.html.

16 HOW SUPPLIED/STORAGE AND HANDLING

Cyclophosphamide Injection, 100 mg/mL is a sterile ready-to-dilute, clear, colorless to pale-yellow solution in a multiple-dose vial available in the following strengths:

Strength | NDC Number | Volume
500 mg/5 mL | 0781-3528-10 | Carton of one 5 mL Multiple-Dose Vial
1,000 mg/10 mL | 0781-3529-10 | Carton of one 10 mL Multiple-Dose Vial
2,000 mg/20 mL | 0781-3530-10 | Carton of one 20 mL Multiple-Dose Vial

Store vials refrigerated at 2°C to 8°C (36°F to 46°F).

Cyclophosphamide is a hazardous product. Follow special handling and disposal procedures.1

17 PATIENT COUNSELING INFORMATION

Advise the patient of the following:

Myelosuppression, Immunosuppression, Bone Marrow Failure, and Infections

- Inform patients of the possibility of myelosuppression, immunosuppression, and infections. Explain the need for routine blood cell counts. Instruct patients to monitor their temperature frequently and immediately report any occurrence of fever [see Warnings and Precautions (5.1)].

Urinary Tract and Renal Toxicity

- Advise the patient to report urinary symptoms (patients should report if their urine has turned a pink or red color) and the need for increasing fluid intake and frequent voiding [see Warnings and Precautions (5.2)].

Cardiotoxicity

- Inform patients of the possibility of cardiotoxicity (which may be fatal).
- Advise patients to contact a healthcare professional immediately for any of the following: new onset or worsening shortness of breath, cough, swelling of the ankles/legs, palpitations, weight gain of more than 5 pounds in 24 hours, dizziness or loss of consciousness [see Warnings and Precautions (5.3)].

Pulmonary Toxicity

- Warn patients of the possibility of developing non-infectious pneumonitis. Advise patients to report promptly any new or worsening respiratory symptoms [see Warnings and Precautions (5.4)].

Alcohol Content

- Explain to patients the possible effects of the alcohol content in Cyclophosphamide Injection, including possible effects on the central nervous system. Patients in whom alcohol should be avoided or minimized should consider the alcohol content of Cyclophosphamide Injection. Alcohol could impair their ability to drive or use machines immediately after infusion [see Warnings and Precautions (5.7)].

Secondary Malignancies

- Inform patients that there is an increased risk of secondary malignancies with Cyclophosphamide Injection [see Warnings and Precautions (5.5)].

Embryo-Fetal Toxicity

- Inform female patients of the risk to a fetus and potential loss of the pregnancy. Advise females to inform their healthcare provider of a known or suspected pregnancy [see Warnings and Precautions (5.8) and Use in Specific Populations (8.1)].
- Advise females of reproductive potential to use effective contraception during treatment and for up to 1 year after completion of therapy [see Warning and Precautions (5.8) and Use in Specific Population (8.1,8.3)].
- Advise male patients with female partners of reproductive potential to use effective contraception during treatment and for 4 months after completion of therapy [see Warnings and Precautions (5.8) and Use in Specific Populations (8.1,8.3)].

Lactation

- Advise women not to breastfeed during treatment and for 1 week after the last dose of Cyclophosphamide Injection [see Use in Specific Populations (8.2)].

Infertility

- Advise patients that Cyclophosphamide Injection may impair fertility in males and females of reproductive potential [see Warnings and Precautions (5.9) and Use in Specific Populations (8.3, 8.4)].

Common Adverse Reactions

- Explain to patients that side effects such as nausea, vomiting, stomatitis, impaired wound healing, amenorrhea, premature menopause, sterility, and hair loss may be associated with cyclophosphamide administration. Other undesirable effects (including, e.g., dizziness, blurred vision, visual impairment) could affect the ability to drive or use machines [see Adverse Reactions (6.1)].

Hydration and Important Administration Instructions

- Advise the patients that during or immediately after the administration, adequate amounts of fluid are required to reduce the risk of urinary tract toxicity [see Dosage and Administration (2.1)].

Manufactured by FAREVA Unterach GmbH for

Sandoz Inc., Princeton, NJ 08540

PRINCIPAL DISPLAY PANEL – 5 mL Carton

NDC 0781-3528-10 Sterile

Cyclophosphamide Injection

500 mg/5 mL

(100 mg/mL)

Must Dilute Before Intravenous Use

Hazardous Drug

Rx Only

One 5 mL Multiple-Dose Vial

SANDOZ

PRINCIPAL DISPLAY PANEL – 10 mL Carton

NDC 0781-3529-10 Sterile

Cyclophosphamide Injection

1,000 mg/10 mL

(100 mg/mL)

Must Dilute Before Intravenous Use

Hazardous Drug

Rx Only

One 10 mL Multiple-Dose Vial

SANDOZ

PRINCIPAL DISPLAY PANEL – 20 mL Carton

NDC 0781-3530-10 Sterile

Cyclophosphamide Injection

2,000 mg/20 mL

(100 mg/mL)

Must Dilute Before Intravenous Use

Hazardous Drug

Rx Only

One 20 mL Multiple-Dose Vial

SANDOZ